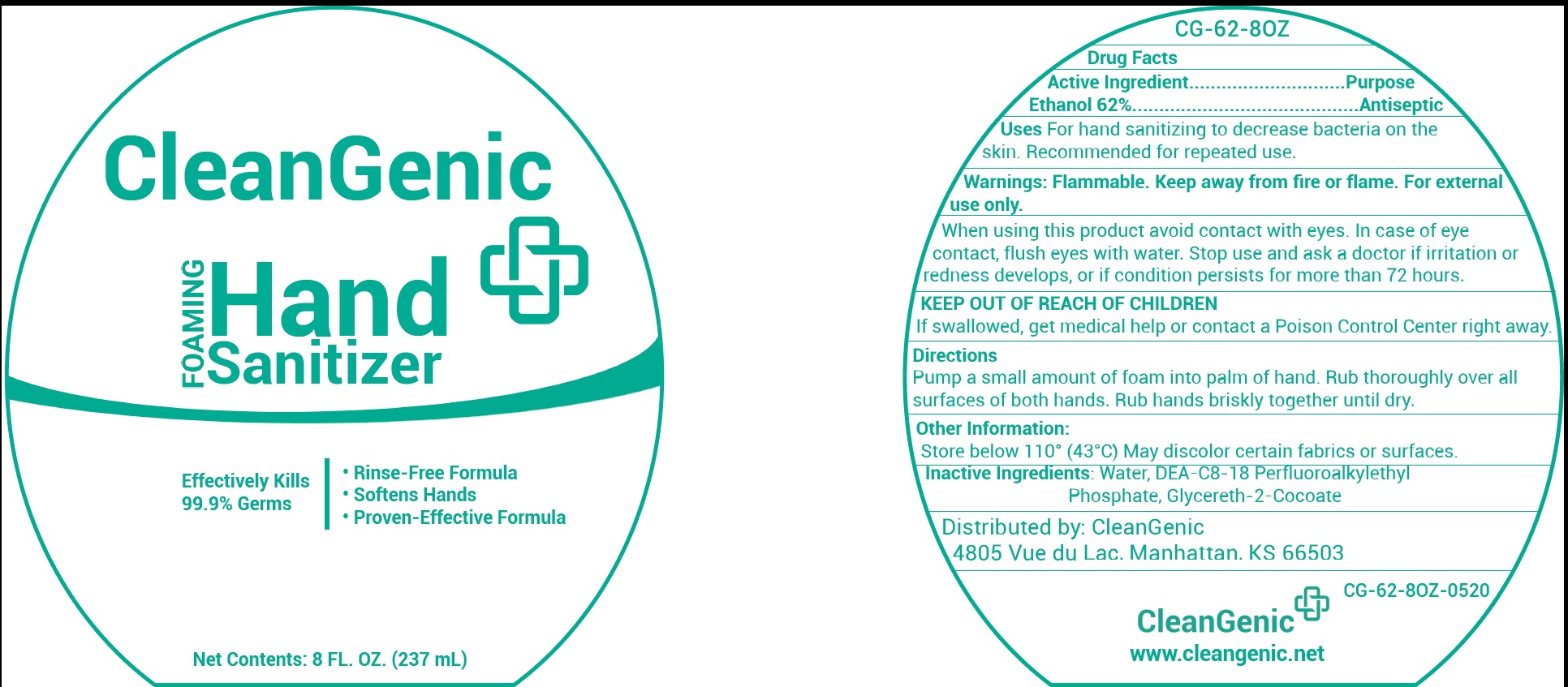 DRUG LABEL: CleanGenic 8 OZ HAND SANITIZER
NDC: 81385-003 | Form: LIQUID
Manufacturer: CleanGenic, LLC
Category: otc | Type: HUMAN OTC DRUG LABEL
Date: 20231028

ACTIVE INGREDIENTS: ALCOHOL 62 mL/100 mL
INACTIVE INGREDIENTS: WATER; DIETHANOLAMINE BIS(C8-C18 PERFLUOROALKYLETHYL)PHOSPHATE; GLYCERETH-2 COCOATE

CleanGenic 8 OZ HAND SANITIZER

Active Ingredient

Ethanol 62%

Purpose

Antiseptic

Uses

For hand sanitizing to decrease bacteria on the skin. Recommended for repeated use.

Warnings:

Flammable, keep away from fire or flame. For external use only.

When using this product

avoid contact with eyes. In case of eye contact, flush eyes with water.

Stop use and ask a doctor if

irritation or redness develops, or if condition persists for more than 72 hours.

KEEP OUT OF REACH OF CHILDREN

If swallowed, get medical help or contact a Poison Control Center right away.

Directions

Pump a small amount of foam into palm of hand. Rub thoroughly over all surfaces of both hands. Rub hands briskly together until dry.

Other Information:

Store below 110° (43°C) May discolor certain fabrics or surfaces.

Inactive Ingredients:

Water, DEA-C8-18 Perfluoroalkylethyl Phosphate, Glycereth-2-Cocoate